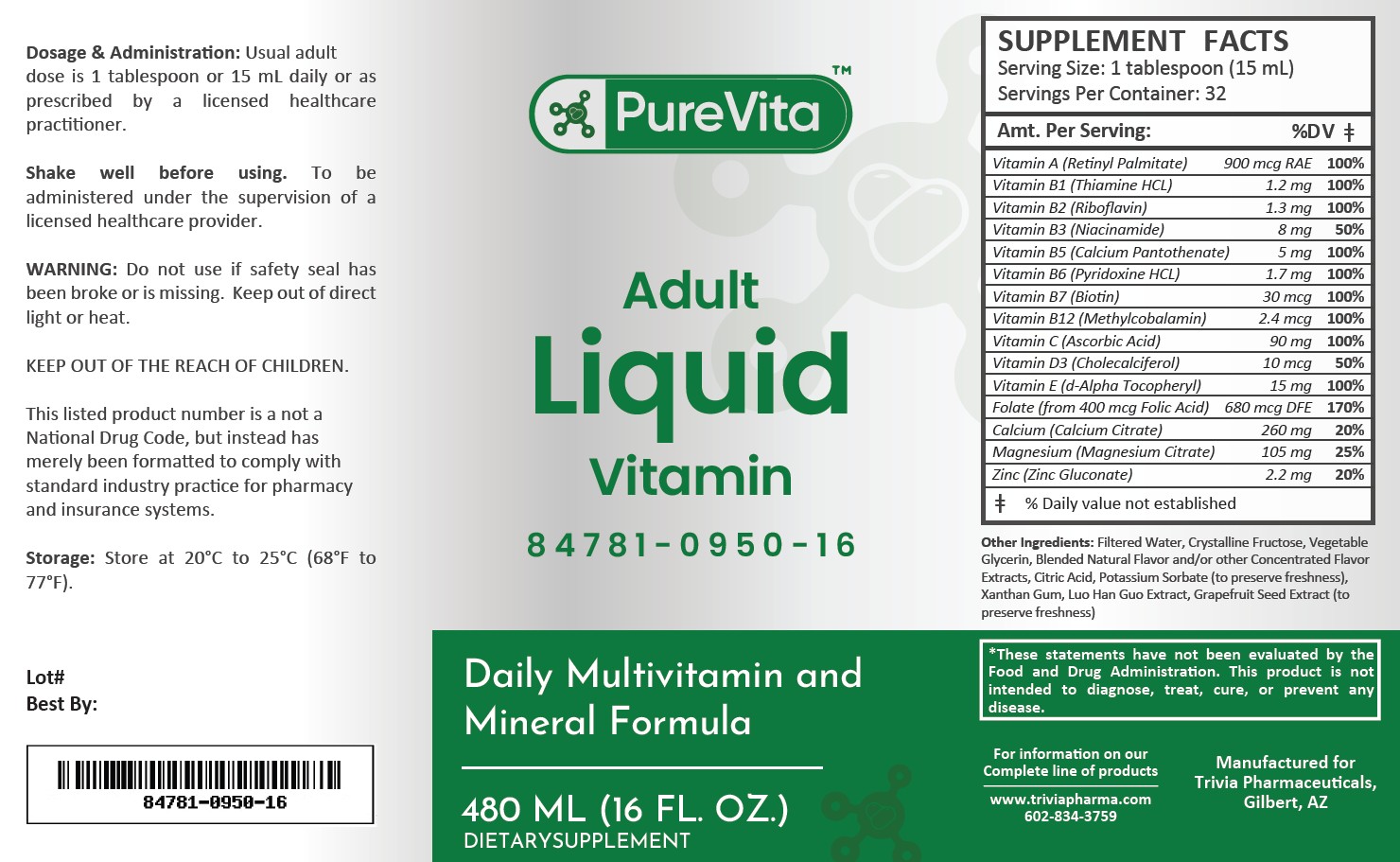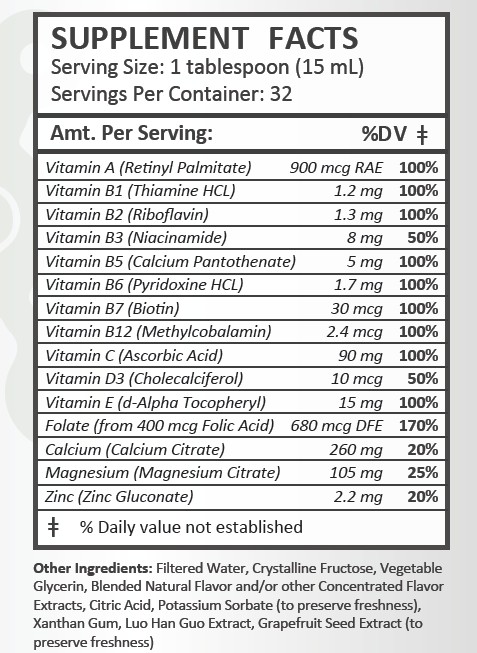 DRUG LABEL: PureVita Adult
NDC: 84781-950 | Form: LIQUID
Manufacturer: Trivia Pharmaceuticals, LLC
Category: other | Type: Dietary Supplement
Date: 20250318

ACTIVE INGREDIENTS: VITAMIN A ACETATE 900 ug/15 mL; THIAMINE HYDROCHLORIDE 1.2 mg/15 mL; RIBOFLAVIN 1.3 mg/15 mL; NIACINAMIDE 8 mg/15 mL; PANTOTHENIC ACID 5 mg/15 mL; PYRIDOXINE HYDROCHLORIDE 1.7 mg/15 mL; BIOTIN 30 ug/15 mL; METHYLCOBALAMIN 2.4 ug/15 mL; ASCORBIC ACID 90 mg/15 mL; CHOLECALCIFEROL 10 ug/15 mL; .ALPHA.-TOCOPHEROL, D- 15 mg/15 mL; FOLIC ACID 680 ug/15 mL; CALCIUM CITRATE 260 mg/15 mL; MAGNESIUM CITRATE 105 mg/15 mL; ZINC GLUCONATE 2.2 mg/15 mL

PureVita Adult Liquid Multivitamin

Health Claim:

PureVita Adult Liquid Vitamin

Description:

PureVita Adult liquid vitamin is indicated to provide significant amounts of essential vitamins and minerals, including Vitamins A, C, D, E, thiamine, riboflavin, niacin, vitamin B6, vitamin B12, folate, calcium, magnesium, and zinc, to supplement the diet. This comprehensive nutrient profile helps prevent nutritional deficiencies of these vitamins and minerals, ensuring that the specific dietary needs of adults and children are met to support overall health, energy, and vitality. The product is specially formulated to target common vitamin and mineral gaps in adults, thus promoting optimal health, immune function, bone strength, and metabolic balance. It is intended to be used under the guidance of a licensed healthcare practitioner to ensure that any potential for nutritional deficiency is addressed in a manner that supports the individual's overall health and wellbeing.

PureVita Adult Liquid Vitamin should be administered under the supervision of a licensed medical practitioner.

This listed product is not a National Drug Code, but instead has merely been formatted to comply with standard industry practice for pharmacy and insurance computer systems.

Warning and Precautions:

This product is contraindicated in patients with a known hypersensitivity to any of the ingredients.

PureVita Adult Liquid Vitamin should only be used under the direction and supervision of a licensed medical practitioner. Use with caution in patients that may have a medical condition, are pregnant, lactating, trying to conceive, under the age of 18, or taking medications.

Dosage and Adminstration:

PureVita Liquid Multivitamin for Adults: The usual adult dose is 1 tablespoon (15 mL) daily.

How Supplied:

PureVita Adult Liquid Vitamin is supplied in a 16 fl. oz. bottle.

84781-0950-16

Reserved for Professional Recommendation

All prescriptions using this product shall be pursuant to state statutes as applicable. This is not an Orange Book product. This product may be administered only under a physician’s supervision. There are no implied or explicit claims on therapeutic equivalence.

Manufactured for:
Trivia Pharmaceuticals

Gilbert, AZ

Storage:

Do not use if bottle seal is broken.
KEEP THIS AND ALL MEDICATIONS OUT OF THE REACH OF CHILDREN.
Store at controlled room temperature 20° to 25°C (68° to 77°F). [See USP guidlelines].
Protect from light and moisture and avoid excessive heat.